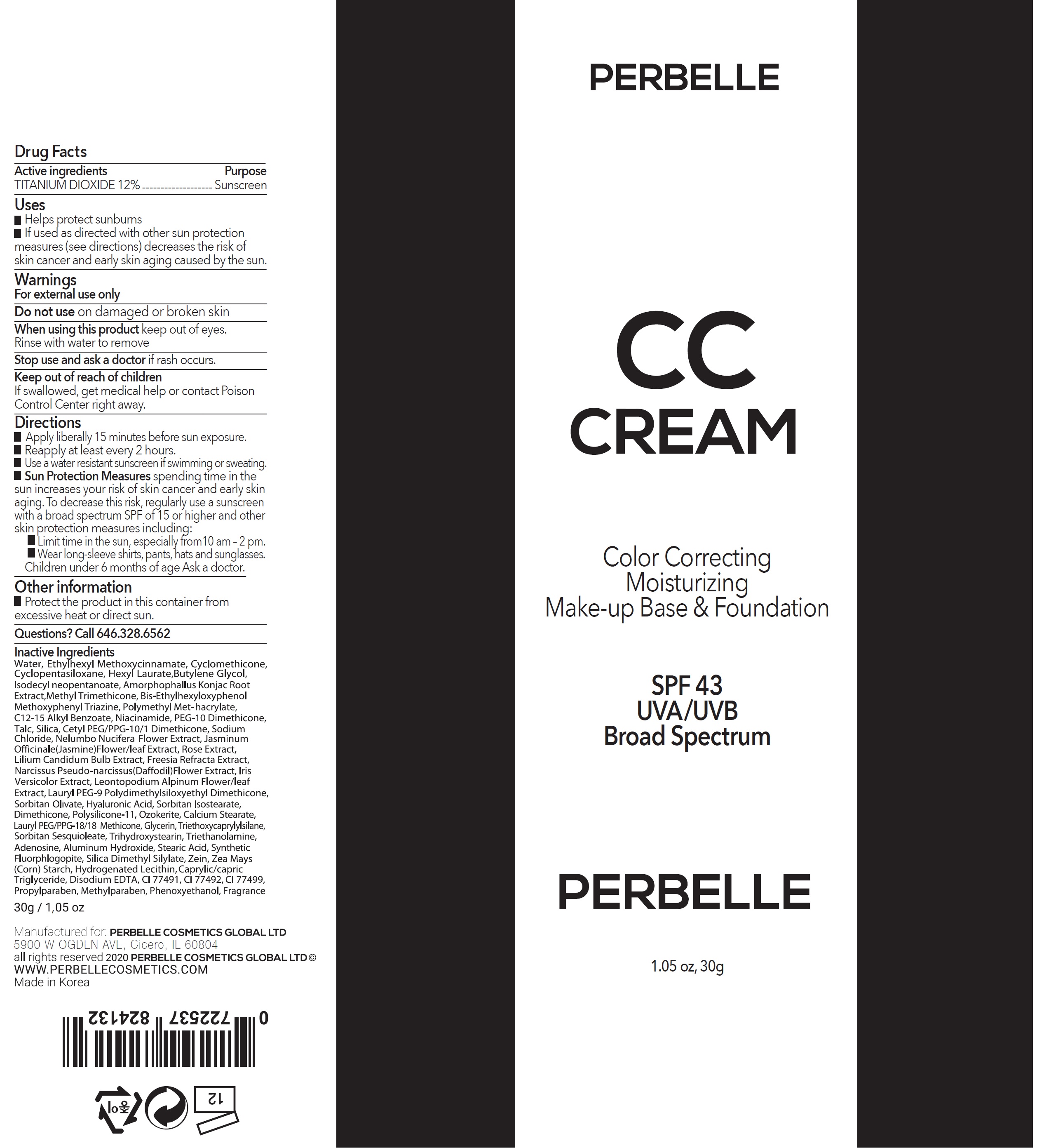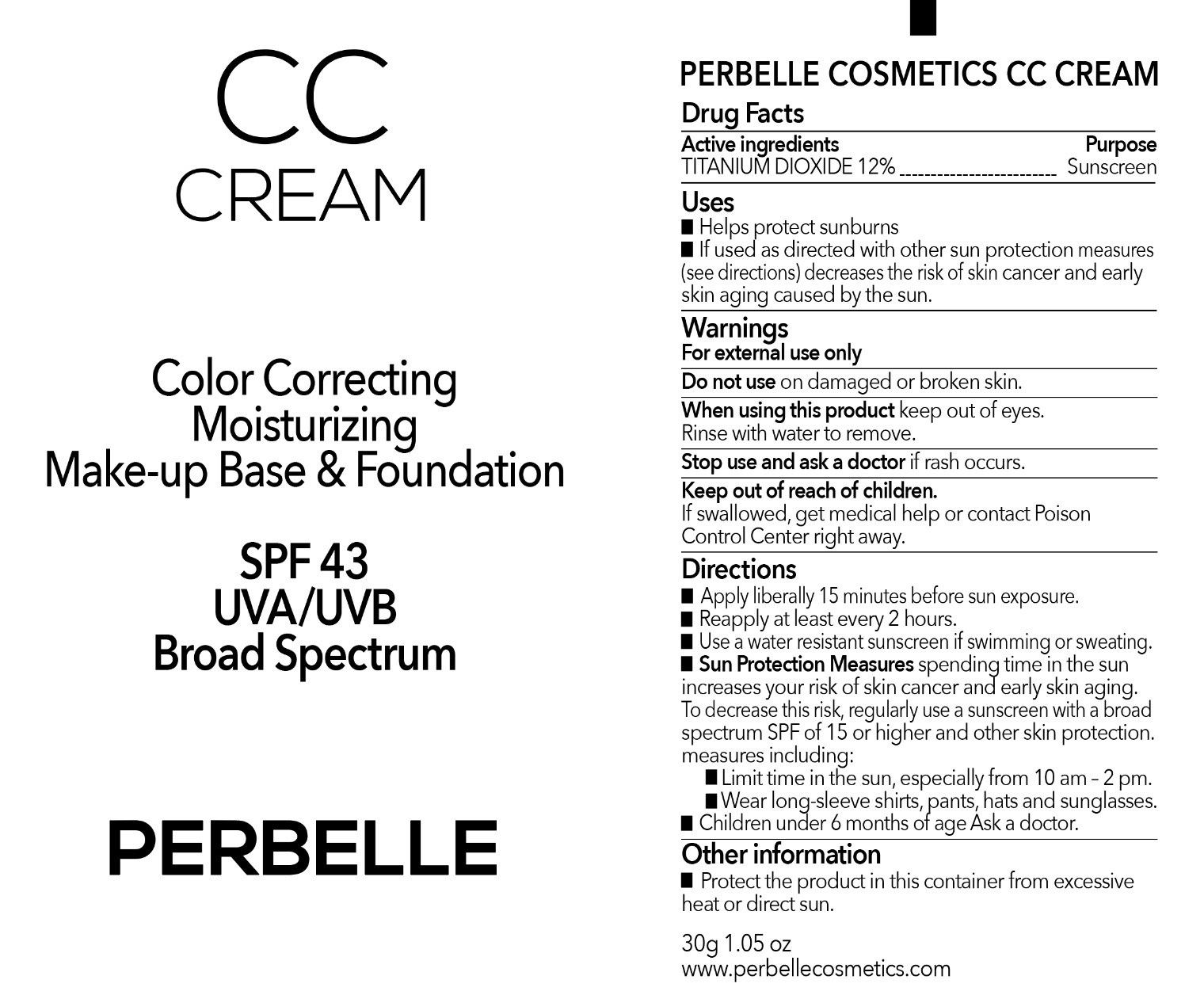 DRUG LABEL: Perbelle CC SPF43 UVA UVB Broad Spectrum
NDC: 81186-000 | Form: CREAM
Manufacturer: Perbelle Cosmetics Global Ltd.
Category: otc | Type: HUMAN OTC DRUG LABEL
Date: 20231201

ACTIVE INGREDIENTS: TITANIUM DIOXIDE 120 mg/1 g
INACTIVE INGREDIENTS: FERRIC OXIDE YELLOW; FERROSOFERRIC OXIDE; PROPYLPARABEN; METHYLPARABEN; PHENOXYETHANOL; WATER; OCTINOXATE; CYCLOMETHICONE; CYCLOMETHICONE 5; HEXYL LAURATE; BUTYLENE GLYCOL; ISODECYL NEOPENTANOATE; AMORPHOPHALLUS KONJAC ROOT; METHYL TRIMETHICONE; BEMOTRIZINOL; POLY(METHYL METHACRYLATE; 450000 MW); ALKYL (C12-15) BENZOATE; NIACINAMIDE; PEG-10 DIMETHICONE (600 CST); TALC; SILICON DIOXIDE; SODIUM CHLORIDE; NELUMBO NUCIFERA FLOWER; JASMINUM OFFICINALE FLOWER; LILIUM CANDIDUM BULB; IRIS VERSICOLOR ROOT; LEONTOPODIUM NIVALE SUBSP. ALPINUM FLOWERING TOP; LAURYL PEG-9 POLYDIMETHYLSILOXYETHYL DIMETHICONE; SORBITAN OLIVATE; HYALURONIC ACID; SORBITAN ISOSTEARATE; DIMETHICONE; CALCIUM STEARATE; LAURYL PEG/PPG-18/18 METHICONE; GLYCERIN; TRIETHOXYCAPRYLYLSILANE; SORBITAN SESQUIOLEATE; TRIHYDROXYSTEARIN; TROLAMINE; ADENOSINE; ALUMINUM HYDROXIDE; STEARIC ACID; MAGNESIUM POTASSIUM ALUMINOSILICATE FLUORIDE; SILICA DIMETHYL SILYLATE; ZEIN; STARCH, CORN; MEDIUM-CHAIN TRIGLYCERIDES; EDETATE DISODIUM ANHYDROUS; FERRIC OXIDE RED

Perbelle CC Cream SPF43 UVA/UVB Broad Spectrum

Active ingredients

TITANIUM DIOXIDE 12%

Purpose

Sunscreen

Uses

- Helps protect sunburns
- If used as directed with other sun protection measures (see directions) decreases the risk of skin cancer and early skin aging caused by the sun.

Warnings

For external use only

Do not use

on damaged or broken skin

When using this product

keep out of eyes. Rinse with water to remove

Stop use and ask a doctor

if rash occurs.

Keep out of reach of children

If swallowed, get medical help or contact Poison Control Center right away.

Directions

- Apply liberally 15 minutes before sun exposure.
- Reapply at least every 2 hours.
- Use a water reistant sunscreen if swimming or sweating.
- spending time in the sun increases your risk of skin cancer and early skin aging. To decrese this risk, regularly use a sunscreen with a broad spectrum SPF of 15 or higher and other skin protection measures including: Sun Protection Measures
- Limit time in the sun, especially from 10 am - 2 pm.
- Wear long-sleeve shirts, pants, hats and sunglasses. Children under 6 months of age Ask doctor.

Other information

- Protect the product in this container from excessive heat or direct sun.

Questions?

Call 646.328.6562

Inactive Ingredient

Water, Ethylhexyl methoxycinnamte, Cyclomethicone, Cyclopentasiloxane, Hexyl Laurate, Butylene Glycol, Isodecyl neopentanoate, Amorphophallus Konjac Root Extract, Methyl Trimethicone, Bis-Ethylhexlyoxyphenol Methoxypehnyl Triazine, Polymethyl Met-hacrylate, C12-15 Alkyl Benzoate, Niacinamide, PEG-10 Dimethicone, Talc, Silica, Cetyl PEG/PPG-10/1 Dimethicone, Sodium Chloride, Nelumbo Nucifera Flower Extract, Jasminum Officinale (Jasmine) Flower/leaf Extract, Rose Extract, Lilium Candidum Bulb Extract, Freesia Refracta Extract, Iris Versicolor Extract, Leontopodium Alpinum Flower/leaf Extract, Lauryl PEG-9 Polydimethylsiloxyethyl Dimethicone, Sorbitan Olivate, Hyaluronic Acid, Sorbitan Isostearate, Dimethicone, Polysilicone-11, Ozokerite, Calcium Stearate, Lauryl PEG/PPG-18/18 Methicone, Glycerin, Triethoxycaprylylylsilane, Sorbitan Sesquioleate, Trihydroxysteain, Triethanolamine, Adenosine, Aluminum Hydroxide, Stearic Acid, Synthetic Fluorphlogopite, Silica Dimethyl Silylate, Zein, Zea Mays (Corn) Strach, Hydrogented Lecithin, Caprylic/capric Triglyceride, Disodium EDTA, CI 77491, CI 77492, CI 77499, Propylparaben, Methylparaben, Phenoxyethanol, Fragrance